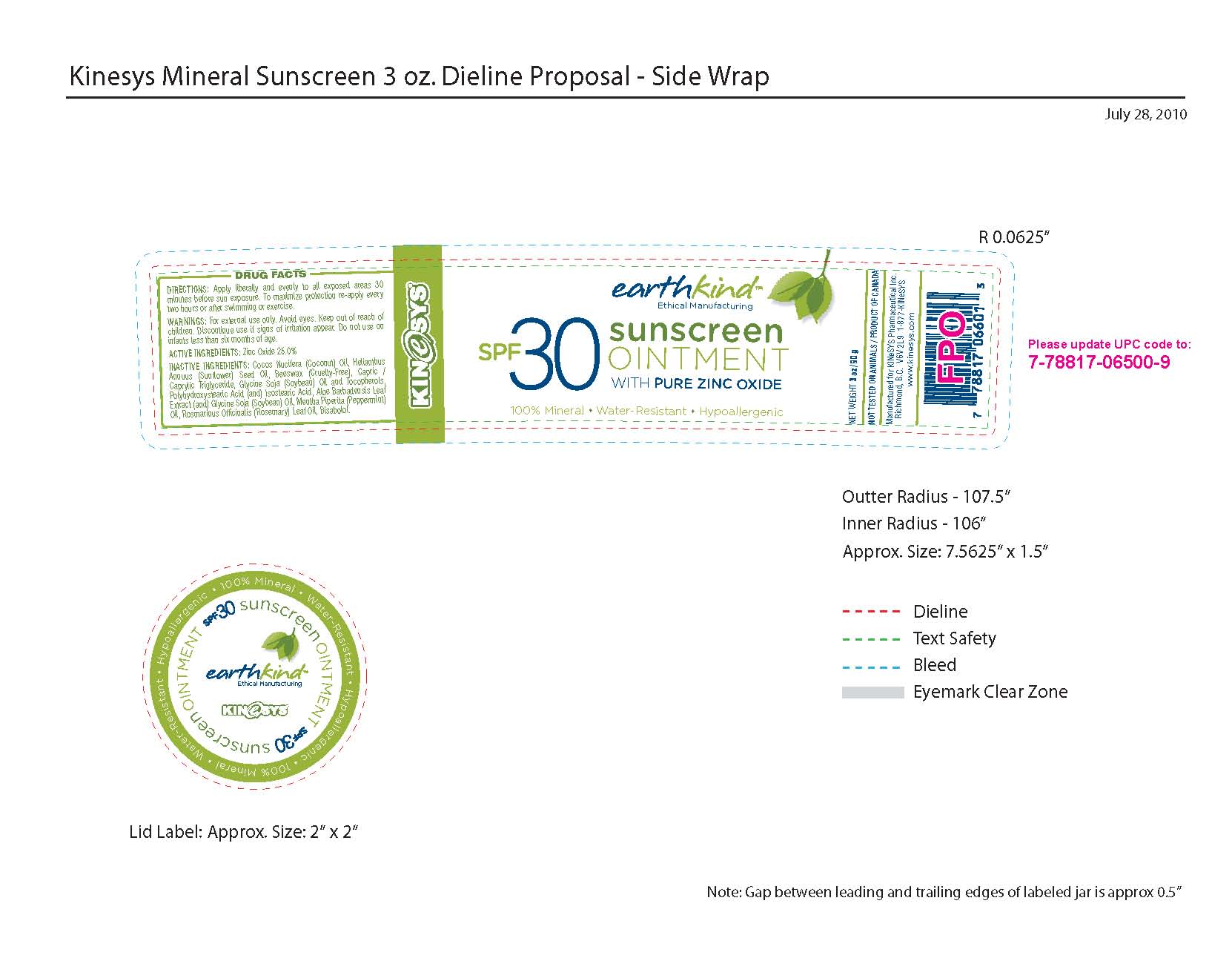 DRUG LABEL: KINeSYS EarthKind SPF 30 Sunscreen
NDC: 61481-0037 | Form: OINTMENT
Manufacturer: KINeSYS Pharmaceutical Inc.
Category: otc | Type: HUMAN OTC DRUG LABEL
Date: 20110215

ACTIVE INGREDIENTS: ZINC OXIDE 250 g/1000 g
INACTIVE INGREDIENTS: COCONUT OIL; SUNFLOWER OIL; YELLOW WAX; TRICAPRIN; SOYBEAN OIL; ALPHA-TOCOPHEROL; POLYHYDROXYSTEARIC ACID (2300 MW); GLYCERYL ISOSTEARATE; ALOE VERA LEAF; PEPPERMINT OIL; ROSEMARY OIL; LEVOMENOL

WARNINGS

WARNINGS: For External Use only. Avoid Eyes. Keep out of reach of children. Discontinue use if signs of irritation appear. Do not use on infants less than six months of age.

ACTIVE INGREDIENTS: Zinc Oxide 25.0%

Package Label